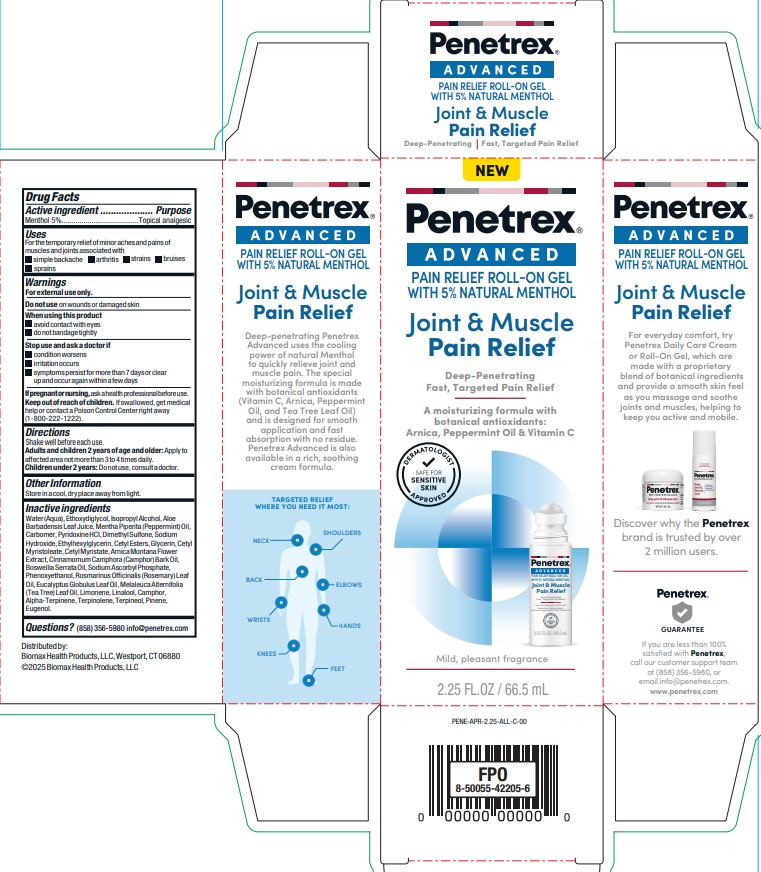 DRUG LABEL: Advanced Pain Relief Roll-On Gel With 5% Natural Menthol
NDC: 62742-4279 | Form: GEL
Manufacturer: Allure Labs
Category: otc | Type: HUMAN OTC DRUG LABEL
Date: 20260225

ACTIVE INGREDIENTS: MENTHOL 5 g/100 g
INACTIVE INGREDIENTS: CINNAMOMUM CAMPHORA (CAMPHOR) BARK OIL; EUCALYPTUS GLOBULUS LEAF OIL; ISOPROPYL ALCOHOL; CARBOMER; PINENE; SODIUM HYDROXIDE; MENTHA PIPERITA (PEPPERMINT) OIL; CETYL ESTERS; GLYCERIN; PYRIDOXINE HCL; ETHYLHEXYLGLYCERIN; BOSWELLIA SERRATA OIL; CETYL MYRISTOLEATE; ARNICA MONTANA FLOWER; PHENOXYETHANOL; ROSMARINUS OFFICINALIS (ROSEMARY) LEAF OIL; TERPINOLENE; TERPINEOL; ALOE BARBADENSIS LEAF JUICE; DIMETHYL SULFONE; CETYL MYRISTATE; LINALOOL, (+)-; ALPHA-TERPINENE; SODIUM ASCORBYL PHOSPHATE; WATER; ETHOXYDIGLYCOL; CAMPHOR (NATURAL); EUGENOL; MELALEUCA ALTERNIFOLIA (TEA TREE) LEAF OIL; LIMONENE, (+)-

Drug Facts

Active ingredient : Menthol 5%

Purpose: Topical analgesic

Uses:

For the temporary relief of minor aches and pains of muscles and joints associated with

simple backache

arthritis

strains

bruises

sprains

Warnings:

For external use only.

Do not use on wounds or damaged skin

When using this product

avoid contact with eyes

do not bandage tight

Stop use and ask a doctor if

condition worsens

irritation occurs

symptoms persist for more than 7 days or clear up and occur again within a few days

Keep out of reach of children. If swallowed, get medical help or contact a Poison Control Center right away

DOSAGE AND ADMINISTRATION

Directions:Shake well before each use.

Adults and children 2 years of age and older: Apply to affected area not more than 3 to 4 times daily.

Children under 2 years: Do not use, consult a doctor.

Other Information:

If pregnant or nursing, ask a health professional before use.

Store in a cool, dry place away from light

Inactive ingredients:

Water (Aqua), Ethoxydiglycol, Isopropyl Alcohol, Aloe Barbadensis Leaf Juice, Mentha Piperita (Peppermint) Oil, Carbomer, Pyridoxine HCI, Dimethyl Sulfone, Sodium Hydroxide, Ethylhexylglycerin, Cetyl Esters, Glycerin, Cetyl Myristoleate, Cetyl Myristate, Arnica Montana Flower Extract, Cinnamomum Camphora (Camphor) Bark Oil, Boswellia Serrata Oil, Sodium Ascorbyl Phosphate, Phenoxyethanol, Rosmarinus Officinalis (Rosemary) Leaf Oil, Eucalyptus Globulus Leaf Oil, Melaleuca Alternifolia (Tea Tree) Leaf Oil, Limonene, Linalool, Camphor, Alpha-Terpinene, Terpinolene, Terpineol, Pinene, Eugenol.